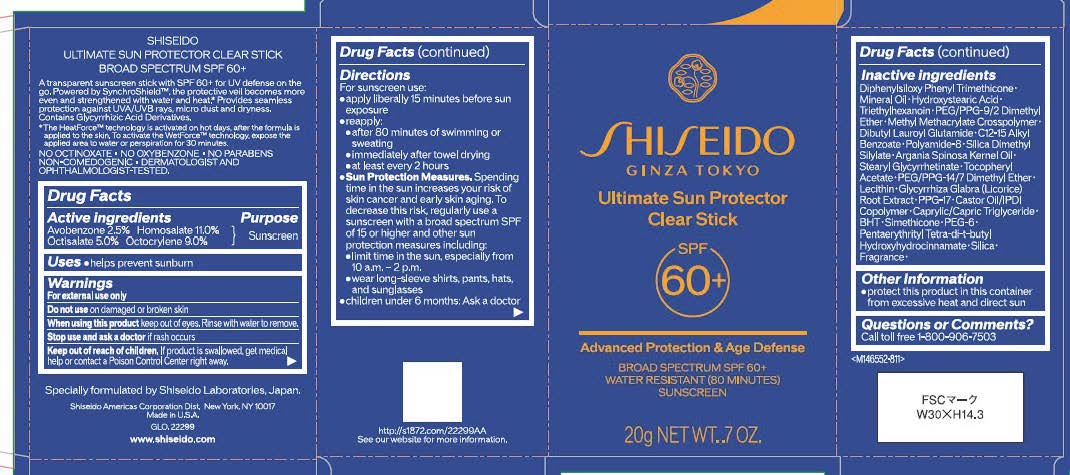 DRUG LABEL: SHISEIDO ULTIMATE SUN PROTECTOR CLEAR
NDC: 58411-969 | Form: STICK
Manufacturer: Shiseido Americas Corporation
Category: otc | Type: HUMAN OTC DRUG LABEL
Date: 20260130

ACTIVE INGREDIENTS: AVOBENZONE 0.5 g/19.98 mL; HOMOSALATE 2.2 g/19.98 mL; OCTISALATE 1 g/19.98 mL; OCTOCRYLENE 1.8 g/19.98 mL
INACTIVE INGREDIENTS: DIPHENYLSILOXY PHENYL TRIMETHICONE; MINERAL OIL; HYDROXYSTEARIC ACID; TRIETHYLHEXANOIN; PEG/PPG-9/2 DIMETHYL ETHER; DIBUTYL LAUROYL GLUTAMIDE; C12-15 ALKYL BENZOATE; ARGANIA SPINOSA KERNEL OIL; STEARYL GLYCYRRHETINATE; .ALPHA.-TOCOPHEROL ACETATE; PEG/PPG-14/7 DIMETHYL ETHER; SOYBEAN LECITHIN; GLYCYRRHIZA GLABRA (LICORICE) ROOT; PPG-17; CASTOR OIL/IPDI COPOLYMER; CAPRYLIC/CAPRIC TRIGLYCERIDE; BHT; DIMETHICONE, UNSPECIFIED; PEG-6; PENTAERYTHRITYL TETRA-DI-T-BUTYL HYDROXYHYDROCINNAMATE; SILICA

SHISEIDO ULTIMATE SUN PROTECTOR CLEAR

Drug Facts

Active Ingredients |  | Purpose
AVOBENZONE 2.5% | HOMOSALATE 11% | Sunscreen
OCTISALATE 5% | OCTOCRYLENE 9% | Sunscreen

Uses

- helps prevent sunburn

Warnings

For external use only

Do not useon damaged or broken skin

WHEN USING

When using this productkeep out of eyes. Rinse with water to remove.

Stop use and ask a doctorif rash occurs

Keep out of reach of children.If product is swallowed, get medical help or contact a Poison Control Center right away.

Directions

For sunscreen use:

- apply liberally 15 minutes before sun exposure
- reapply:
- after 80 minutes of swimming or sweating
- immediately after towel drying
- at least every 2 hours
- Sun Protection Measures. Spending time in the sun increases your risk of skin cancer and early skin aging. To decrease this risk, regularly use a sunscreen with a broad spectrum SPF of 15 or higher and other sun protection measures including:
- limit time in the sun, especially from 10 a.m. - 2p.m.
- wear long-sleeve shirts, pant, hats, and sunglasses
- children under 6 months: Ask a doctor

INACTIVE INGREDIENT

Diphenylsiloxy Phenyl Trimethicone･Mineral Oil･Hydroxystearic Acid･Triethylhexanoin･PEG/PPG-9/2 Dimethyl Ether･Methyl Methacrylate Crosspolymer･Dibutyl Lauroyl Glutamide･C12-15 Alkyl Benzoate･Polyamide-8･Silica Dimethyl Silylate･Argania Spinosa Kernel Oil･Stearyl Glycyrrhetinate･Tocopheryl Acetate･PEG/PPG-14/7 Dimethyl Ether･Lecithin･Glycyrrhiza Glabra (Licorice) Root Extract･PPG-17･Castor Oil/IPDI Copolymer･Caprylic/Capric Triglyceride･BHT･Simethicone･PEG-6･Pentaerythrityl Tetra-di-t-butyl Hydroxyhydrocinnamate･Silica･Fragrance･

Other Information

- protect this product in this container from excessive heat and direct sun.

Questions or Comments?

Call toll free 1-800-906-7503

PRINCIPLE DISPLAY PANNEL 20g OTHER

SHISEIDO'

GINZA TOKYO

Ultimate Sun Protector

Clear Stick

SPF 60+

Advanced Protection & Age Defense

BROAD SPECTRUM SPF 60+

WATER RESISTANT (80 MINUTES)

SUNSCREEN

20g NET WT..7 OZ.